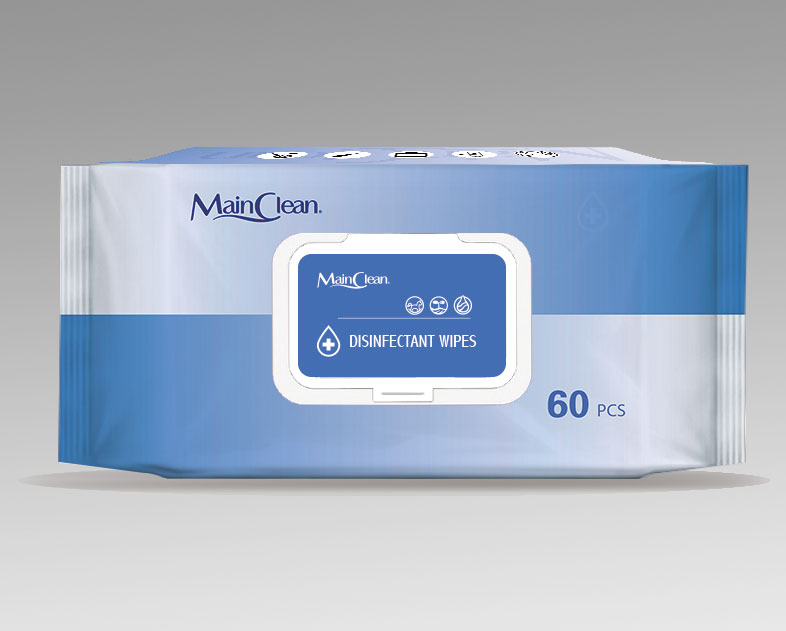 DRUG LABEL: MainClean Disinfectant Wipes 11060208
NDC: 75162-2011 | Form: PATCH
Manufacturer: Shandong Mainclean Medical Products Co., Ltd.
Category: otc | Type: HUMAN OTC DRUG LABEL
Date: 20200420

ACTIVE INGREDIENTS: ALCOHOL 15 1/100 1
INACTIVE INGREDIENTS: PROPYLENE GLYCOL 0.25 1/100 1; WATER 84.585 1/100 1; CETYLPYRIDINIUM CHLORIDE ANHYDROUS 0.075 1/100 1; PHENOXYETHANOL 0.05 1/100 1; GLYCERIN 0.025 1/100 1; ETHYLHEXYLGLYCERIN 0.015 1/100 1

MainClean, Disinfectant Wipes, *60

Active ingredient

Alcohol, 15% v/v, antiseptic

Inactive ingredient

Cetylpyridinium Chloride

Propylene Glycol

Phenoxyethanol

Glycerin

Ethylhexylglycerin

Water

Purpose

This product is used to wipe hands, faces, skins, etc. It can also be used to clean many kinds of places.

When using

This product is used to wipe hands, faces, skins, etc. It can also be used to clean many kinds of places.

Do not use

Use only as directed.
Do not use for cases not directed.

Stop use

Stop use if the product's volatile gases cause discomfort, or if you experience respiratory irritation such as cough, asthma, or difficulty breathing.

Keep out of reach of children

Indications & usage

This product is used to wipe hands, faces, skins, etc. It can also be used to clean many kinds of places.

Dosage & administration

Use it as needed, after following the usage instructions.

For external use only.

Warnings

Do not apply this product to red and swollen skin, wound or any part sensitive to it.
Keep this product out of children’s reach in case they might eat it.
Do not throw this product into the toilet as it cannot dissolve.